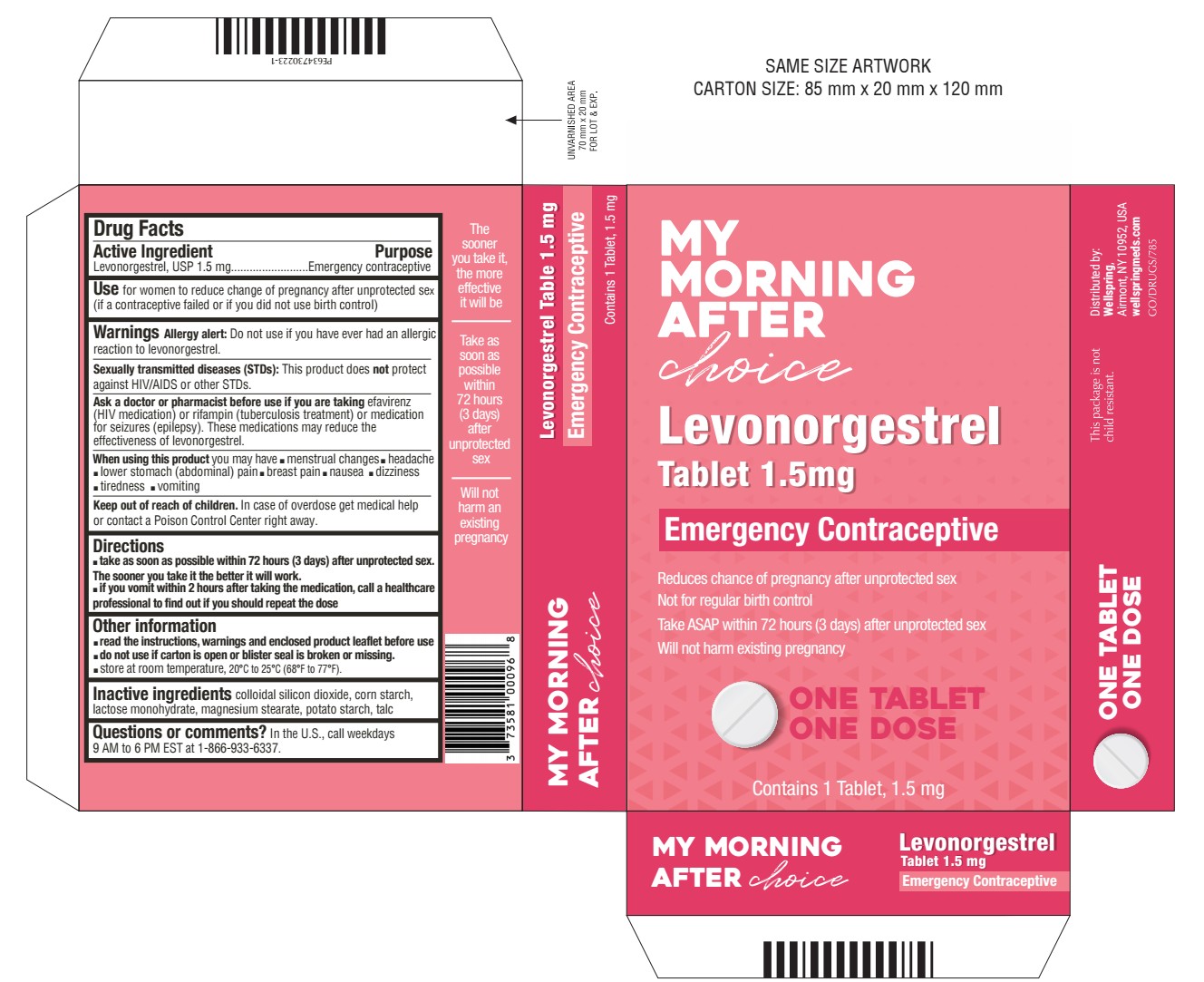 DRUG LABEL: Levonorgestrel
NDC: 73581-217 | Form: TABLET
Manufacturer: YYBA Corp
Category: otc | Type: HUMAN OTC DRUG LABEL
Date: 20260203

ACTIVE INGREDIENTS: LEVONORGESTREL 1.5 mg/1 1
INACTIVE INGREDIENTS: MAGNESIUM STEARATE; STARCH, POTATO; STARCH, CORN; LACTOSE MONOHYDRATE; SILICON DIOXIDE; TALC

Levonorgestrel Glenmark

Active ingredient

Levonorgestrel, USP 1.5mg

Purpose

Emergency contraceptive

Use

For women to reduce chance of pregnancy after unprotected sex (if a contraceptive failed or if you did not use birth control)

Warnings

Allergy alert: Do not use if you have ever had an allergic reaction to levonorgestrel

Sexually transmitted disease (STDs) alert: This product does not protect against HIV/AIDS or other STDs

Do not use

- if you are already pregnant (because it will not work)
- for regular birth control

Ask a doctor or pharmacist before use if you are taking efavirenz (HIV medication) or rifampin (tuberculosis treatment) or medication for seizures (epilepsy). These medications may reduce the effectiveness of levonorgestrel.

When using this product you may have

- menstrual changes
- nausea
- lower stomach (abdominal) pain
- tiredness
- headache
- dizziness
- breast pain
- vomiting

Keep out of reach of children.

In case of overdose, get medical help or contact a Poison Control Center right away.

Directions

- take as soon as possible within 72 hours (3 days) after unprotected sex.

The sooner you take it the better it will work.

- if you vomit within 2 hours after taking the medication, call a healthcare professional to find out if you should repeat the dose

Other information

- read the instructions, warnings and enclosed product leaflet before use
- this product works mainly by preventing ovulation (egg release). It may also prevent fertilization of a released egg (joining of sperm and egg) or attachment of a fertilized egg to the uterus (implantation).
- do not use if carton is open or tear strip is removed or blister seal is broken or missing
- Store at room temperature, 20°C to 25°C (68°F to 77°F)

Inactive ingredients

Colloidal silicon dioxide, corn starch, lactose monohydrate, magnesium stearate, potato starch, talc

Questions or comments?

In the U.S., call weekdays 9 AM to 6 PM EST at 1-866-933-6337.

What is Levonorgestrel Tablet?

Levonorgestrel tablet is emergency contraception that helps prevent pregnancy after birth control failure or unprotected sex. It is a backup method of preventing pregnancy and should not be used as regular birth control.

What Levonorgestrel Tablet is not.

Levonorgestrel tablet will not work if you are already pregnant and will not affect an existing pregnancy. Levonorgestrel tablet will not protect you from HIV infection (the virus that causes AIDS) and other sexually transmitted diseases (STDs).

When should I use Levonorgestrel Tablet?

The sooner you take emergency contraception, the better it works. You should use levonorgestrel tablet within 72 hours (3 days)
after you have had unprotected sex
Levonorgestrel tablet is a backup or emergency method of birth control you can use when:

- your regular birth control was used incorrectly or failed
- you did not use any birth control method

When not to use Levonorgestrel Tablet.

- as a regular birth control method, because it’s not as effective as regular birth control.
- if you are already pregnant, because it will not work.
- if you are allergic to levonorgestrel or any other ingredients in Levonorgestrel Tablet.

When should I talk to a doctor or pharmacist?

Ask a doctor or pharmacist before use if you are taking efavirenz (HIV medication) or rifampin (tuberculosis treatment) or medication for seizures (epilepsy). These medications may reduce the effectiveness of levonorgestrel tablet and increase your chance of becoming pregnant. Your doctor may prescribe another form of emergency contraception that may not be affected by these medications.

How does Levonorgestrel Tablet work?

Levonorgestrel tablet is one tablet with levonorgestrel, a hormone that has been used in many birth control pills for several decades. Levonorgestrel tablet contains a higher dose of levonorgestrel than birth control pills, but works in a similar way to prevent pregnancy. It works mainly by stopping the release of an egg from the ovary. It is possible that levonorgestrel tablet may also work by preventing fertilization of an egg (the uniting of sperm with the egg) or by preventing attachment (implantation) to the uterus (womb).

How can I get the best results from Levonorgestrel Tablet?

You have 72 hours (3 days) to try to prevent pregnancy after birth control failure or unprotected sex. <content styleCode="bold">The sooner you take levonorgestrel tablet, the better it works

How effective is Levonorgestrel Tablet?

If levonorgestrel tablet is taken as directed, it can significantly decrease the chance that you will get pregnant. About 7 out of every 8 women who would have gotten pregnant will not become pregnant.

How will I know Levonorgestrel Tablet worked?

You will know levonorgestrel tablet has been effective when you get your next period, which should come at the expected time, or within a week of the expected time. If your period is delayed beyond 1 week, it is possible you may be pregnant. You should get a pregnancy test and follow up with your healthcare professional.

Will I experience any side effects?

- some women may have changes in their period, such as a period that is heavier or lighter or a period that is early or late.
- If your period is more than a week late, you may be pregnant.
- if you have severe abdominal pain, you may have an ectopic pregnancy, and should get immediate medical attention.
- when used as directed, levonorgestrel tablet is safe and effective. Side effects may include changes in your period, nausea, lower stomach (abdominal) pain, tiredness, headache, dizziness, and breast tenderness.
- if you vomit within 2 hours of taking the medication, call a healthcare professional to find out if you should repeat the dose.

Keep out of reach of children:

In case of overdose, get medical help or contact a Poison Control Center right away at 1-800-222-1222.